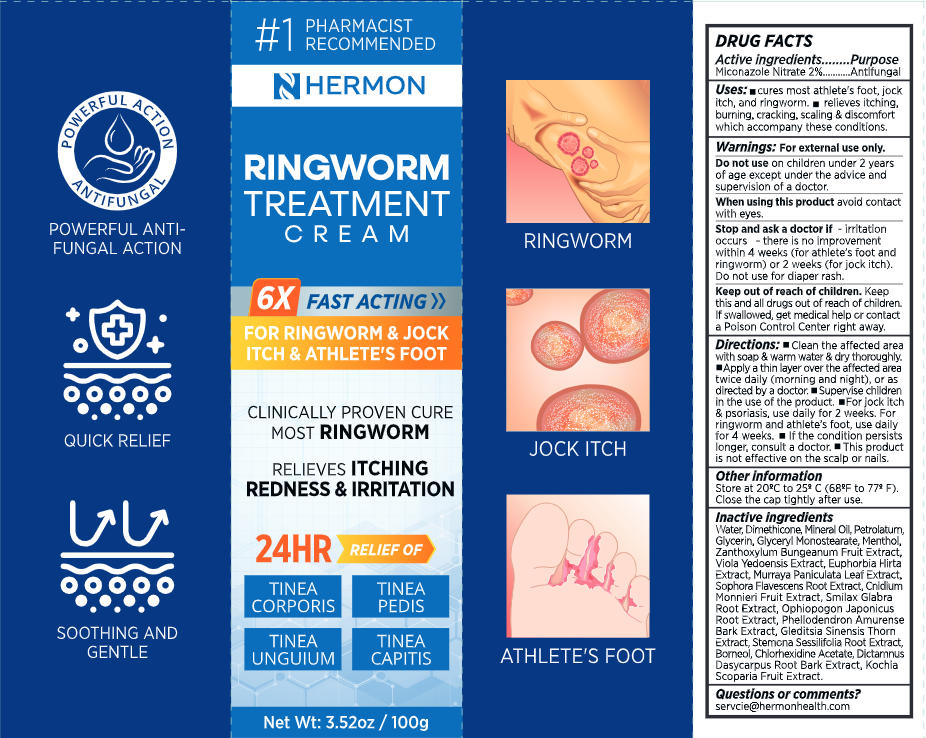 DRUG LABEL: Ringworm Treatment Cream
NDC: 85398-024 | Form: CREAM
Manufacturer: Beautivity LLC
Category: otc | Type: HUMAN OTC DRUG LABEL
Date: 20260110

ACTIVE INGREDIENTS: MICONAZOLE NITRATE 2 g/100 g
INACTIVE INGREDIENTS: MENTHOL; PHELLODENDRON AMURENSE BARK; WATER; DIMETHICONE; ZANTHOXYLUM BUNGEANUM FRUIT; VIOLA PHILIPPICA WHOLE; MURRAYA PANICULATA LEAFY TWIG; SOPHORA FLAVESCENS ROOT; STEMONA SESSILIFOLIA ROOT; GLEDITSIA SINENSIS THORN; EUPHORBIA HIRTA; SMILAX GLABRA WHOLE; OPHIOPOGON JAPONICUS ROOT; DICTAMNUS DASYCARPUS ROOT BARK; GLYCERYL MONOSTEARATE; BORNEOL; CHLORHEXIDINE ACETATE; GLYCERIN; PETROLATUM; CNIDIUM MONNIERI FRUIT; BASSIA SCOPARIA FRUIT; MINERAL OIL

Initial Drug Listing - Hermon Ringworm Treatment Cream

ACTIVE INGREDIENT

Miconazole Nitrate 2%

PURPOSE

Antifungal

DOSAGE AND ADMINISTRATION

- Cures most athlete's foot, jock itch, and ringworm.
- Relieves itching, burning, cracking, scaling & discomfort which accompany these conditions.

WARNINGS

For external use only.

DO NOT USE

on children under 2 years of age except under the advice and supervision of a doctor.

WHEN USING

avoid contact with eyes.

ASK DOCTOR

- Irritation occurs
- There is no improvementwithin 4 weeks (for athlete's foot andringworm) or 2 weeks (for jock itch).
- Do not use for diaper rash.

KEEP OUT OF REACH OF CHILDREN

- Keep this and all drugs out of reach of children.
- If swallowed, get medical help or contacta Poison Control Center right away.

INDICATIONS AND USAGE

- Clean the affected area with soap & warm water & dry thoroughly.
- Apply a thin layer over the affected areatwice daily (morning and night), or asdirected by a doctor.
- Supervise childrenin the use of the product.
- For jock itch& psoriasis, use daily for 2 weeks. Forringworm and athlete's foot, use daily for 4 weeks.
- If the condition persists longer, consult a doctor.
- This productis not effective on the scalp or nails.

OTHER SAFETY INFORMATION

- Store at 20-Cto 25C(68Fto 77eF).
- Close the cap tightly after use.

INACTIVE INGREDIENT

Water, Dimethicone, Mineral Oil, Petrolatum,Glycerin, Glyceryl Monostearate, Menthol,Zanthoxylum Bungeanum Fruit Extract,Viola Yedoensis Extract, Euphorbia Hirta Extract, Murraya Paniculata Leaf Extract,Sophora Flavescens Root Extract, Cnidium Monnieri Fruit Extract, Smilax Glabra Root Extract, Ophiopogon Japonicus Root Extract, Phellodendron AmurenseBark Extract, Gleditsia Sinensis Thorn Extract, Stemona Sessilifolia Root Extract, Borneol, Chlorhexidine Acetate, Dictamnus Dasycarpus Root Bark Extract, Kochia Scoparia Fruit Extract.

NONTERATOGENIC EFFECTS

servcie@hermonhealth.com